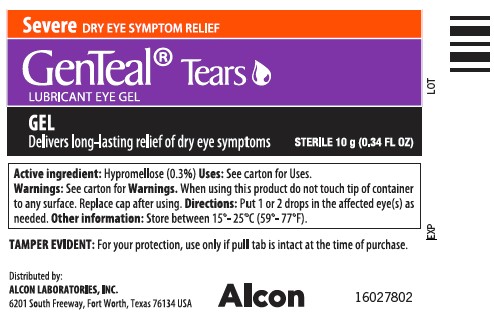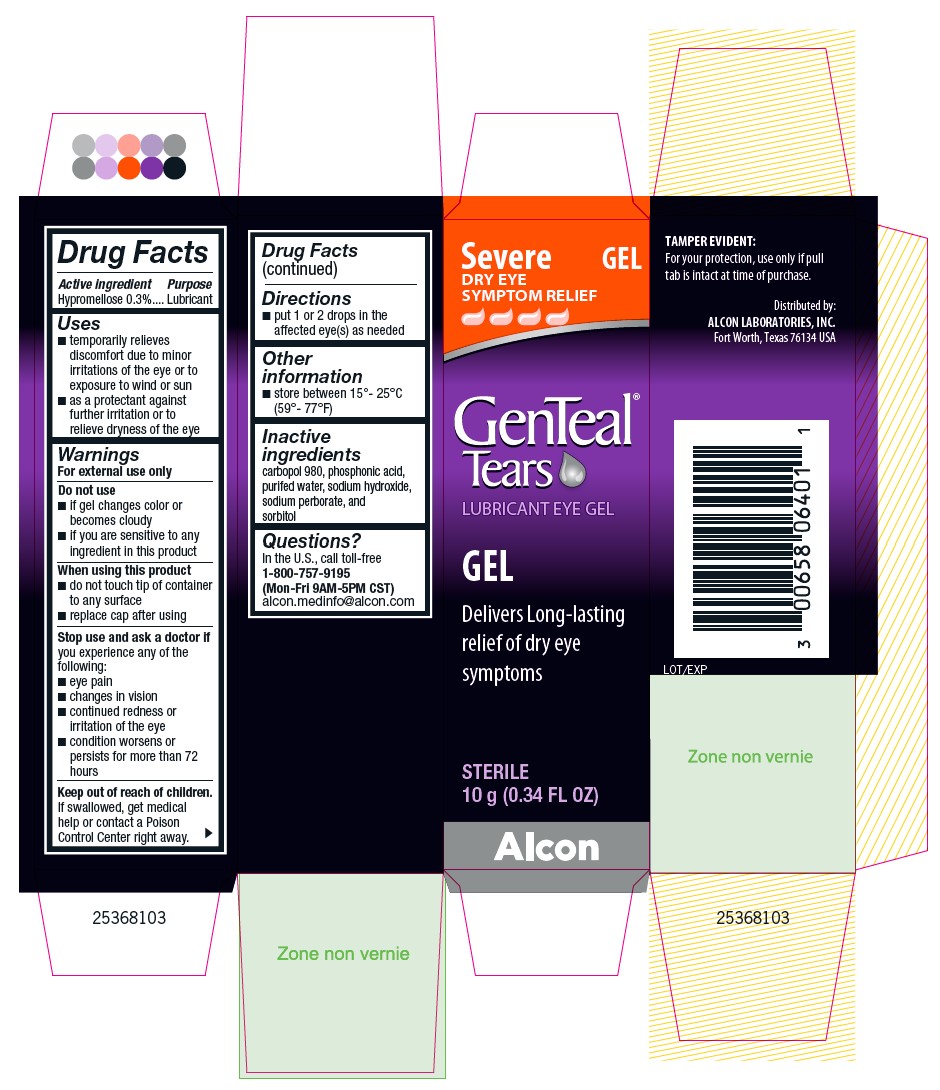 DRUG LABEL: GenTeal Tears 
NDC: 0065-8064 | Form: GEL
Manufacturer: Alcon Laboratories, Inc.
Category: otc | Type: HUMAN OTC DRUG LABEL
Date: 20231214

ACTIVE INGREDIENTS: Hypromellose 2910 (4000 Mpa.S) .003 g/1 g
INACTIVE INGREDIENTS: Sodium Perborate; Phosphonic Acid; Water; Sodium Hydroxide; Sorbitol

Drug Facts

ACTIVE INGREDIENT

Active ingredient | Purpose
Hypromellose 0.3%. | Lubricant

Uses

- temporarily relieves discomfort due to minor irritations of the eye or to exposure to wind or sun
- as a protectant against further irritation or to relieve dryness of the eye

Warnings

For external use only

Do not use

- if gel changes color or becomes cloudy
- if you are sensitive to any ingredient in this product

When using this product

- do not touch tip of container to any surface
- replace cap after using

Stop use and ask a doctor if you experience any of the following:

- eye pain
- changes in vision
- continued redness or irritation of the eye
- condition worsens or persists for more than 72 hours

Keep out of reach of children.

If swallowed, get medical help or contact a Poison Control Center right away.

Directions

- put 1 or 2 drops in the affected eye(s) as needed

Other information

- store between 15º - 25ºC (59º - 77ºF)

Inactive ingredients

carbopol 980, phosphonic acid, purified water, sodium hydroxide, sodium perborate, and sorbitol

Questions?

In the U.S., call toll-free
1-800-757-9195
(Mon-Fri 9AM-5PM CST)
alcon.medinfo@alcon.com

PRINCIPAL DISPLAY PANEL

Severe DRY EYE SYMPTOM RELIEF
GEL
GenTeal® Tears
LUBRICANT EYE GEL
GEL
Delivers Long-lasting relief of dry eye symptoms
STERILE
10 g (0.34 FL OZ)
TAMPER EVIDENT:
For your protection, use only if pull tab is intact at time of purchase.
Distributed by:
ALCON LABORATORIES, INC.
Fort Worth, Texas 76134 USA
Lot/Exp
Alcon
25368103

Severe DRY EYE SYMPTOM RELIEF
GenTeal® Tears
LUBRICANT EYE GEL
GEL
Delivers long-lasting relief of dry eye symptoms
STERILE 10g (0.34 FL OZ)
Active Ingredient: Hypromellose (0.3%) Uses: See carton for Uses.
Warnings: See carton for Warnings. When using this product do not touch tip of container to any surface. Replace cap after using. Directions: Put 1 or 2 drops in the affected eye(s) as needed. Other Information: Store between 15°-25°C (59°-77°F).
TAMPER EVIDENT: For your protection, use only if pull tab is intact at the time of purchase.
Distributed by:
ALCON LABORATORIES, INC.
6201 South Freeway, Fort Worth, Texas 76134 USA
ALCON
16027802